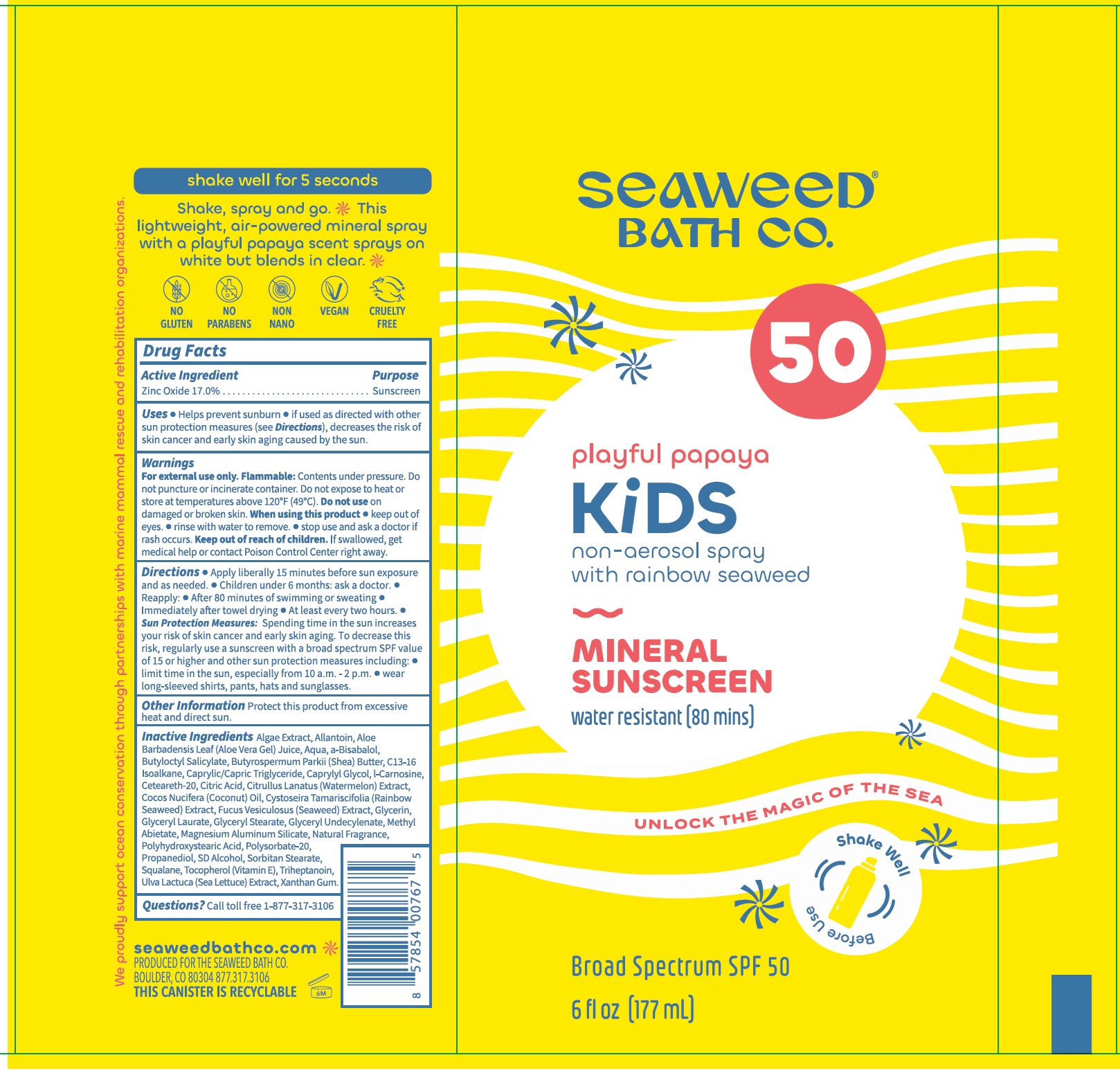 DRUG LABEL: Seaweed Bath Co Playful Papaya Kids Sunscreen SPF 50
NDC: 81159-504 | Form: LIQUID
Manufacturer: The Seaweed Bath Co.
Category: otc | Type: HUMAN OTC DRUG LABEL
Date: 20240619

ACTIVE INGREDIENTS: ZINC OXIDE 170 mg/1 mL
INACTIVE INGREDIENTS: ALLANTOIN; ALOE VERA LEAF; WATER; BUTYLOCTYL SALICYLATE; SHEA BUTTER; C13-16 ISOPARAFFIN; MEDIUM-CHAIN TRIGLYCERIDES; CAPRYLYL GLYCOL; CARNOSINE; POLYOXYL 20 CETOSTEARYL ETHER; CITRIC ACID MONOHYDRATE; WATERMELON; COCONUT OIL; CYSTOSEIRA TAMARISCIFOLIA; FUCUS VESICULOSUS; GLYCERIN; GLYCERYL LAURATE; GLYCERYL MONOSTEARATE; METHYL ABIETATE; MAGNESIUM ALUMINUM SILICATE; POLYSORBATE 20; PROPANEDIOL; SORBITAN MONOSTEARATE; SQUALANE; TOCOPHEROL; TRIHEPTANOIN; ULVA LACTUCA; XANTHAN GUM

Seaweed Bath Co. Playful Papaya Kids Sunscreen SPF 50

Active Ingredient

Zinc Oxide 17.0%

Purpose

Sunscreen

Uses

- Helps prevent sunburn
- if used as directed with other sun protection measures (see Directions), decreases the risk of skin cancer and early skin aging caused by the sun.

Warnings

For external use only.

Flammable: Contents under pressure. Do not puncture or incinerate container. Do not expose to heat or store at temperatures above 120°F (49°C).

Do not use

on damaged or broken skin.

When using this product

- keep out of eyes.
- rinse with water to remove.

stop use and ask a doctor if

rash occurs.

Keep out of reach of children.

If swallowed, get medical help or contact Poison Control Center right away.

Directions

- Apply liberally 15 minutes before sun exposure and as needed.
- Children under 6 months: ask a doctor.
- Reapply:
- After 80 minutes of swimming or sweating
- Immediately after towel drying
- At least every two hours.
- Sun Protection Measures: Spending time in the sun increases your risk of skin cancer and early skin aging. To decrease this risk, regularly use a sunscreen with a broad spectrum SPF value of 15 or higher and other sun protection measures including:
- limit time in the sun, especially from 10 a.m. - 2 p.m.
- wear long-sleeved shirts, pants, hats and sunglasses.

Other Information

Protect this product from excessive heat and direct sun.

Inactive Ingredients

Algae Extract, Allantoin, Aloe Barbadensis Leaf (Aloe Vera Gel) Juice, Aqua, a-Bisabalol, Butyloctyl Salicylate, Butyrospermum Parkii (Shea) Butter, C13-16 Isoalkane, Caprylic/Capric Triglyceride, Caprylyl Glycol, l-Carnosine, Ceteareth-20, Citric Acid, Citrullus Lanatus (Watermelon) Extract, Cocos Nucifera (Coconut) Oil, Cystoseira Tamariscifolia (Rainbow Seaweed) Extract, Fucus Vesiculosus (Seaweed) Extract, Glycerin, Glyceryl Laurate, Glyceryl Stearate, Glyceryl Undecylenate, Methyl Abietate, Magnesium Aluminum Silicate, Natural Fragrance, Polyhydroxystearic Acid, Polysorbate-20, Propanediol, SD Alcohol, Sorbitan Stearate, Squalane, Tocopherol (Vitamin E), Triheptanoin, Ulva Lactuca (Sea Lettuce) Extract, Xanthan Gum.

Questions?

Call toll free 1-877-317-3106